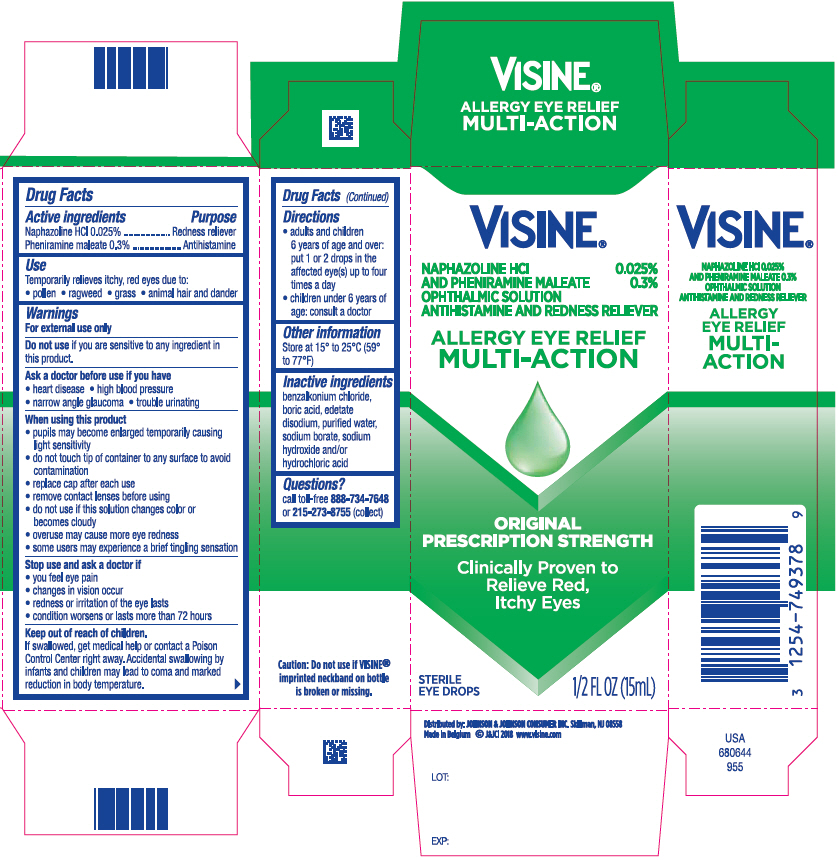 DRUG LABEL: Visine Allergy Eye Relief Multi-Action
NDC: 69968-0367 | Form: SOLUTION/ DROPS
Manufacturer: Kenvue Brands LLC
Category: otc | Type: HUMAN OTC DRUG LABEL
Date: 20241113

ACTIVE INGREDIENTS: NAPHAZOLINE HYDROCHLORIDE 0.25 mg/1 mL; PHENIRAMINE MALEATE 3 mg/1 mL
INACTIVE INGREDIENTS: BENZALKONIUM CHLORIDE; BORIC ACID; EDETATE DISODIUM; WATER; SODIUM BORATE; SODIUM HYDROXIDE; HYDROCHLORIC ACID

Visine® Allergy Eye Relief Multi-Action

Drug Facts

ACTIVE INGREDIENT

Active ingredients | Purpose
Naphazoline HCl 0.025% | Redness reliever
Pheniramine maleate 0.3% | Antihistamine

Uses

Temporarily relieves itchy, red eyes due to:

- pollen
- ragweed
- grass
- animal hair and dander

Warnings

For external use only

Do not use if you are sensitive to any ingredient in this product.

Ask a doctor before use if you have

- heart disease
- high blood pressure
- narrow angle glaucoma
- trouble urinating

When using this product

- pupils may become enlarged temporarily causing light sensitivity
- do not touch tip of container to any surface to avoid contamination
- replace cap after each use
- remove contact lenses before using
- do not use if this solution changes color or becomes cloudy
- overuse may cause more eye redness
- some users may experience a brief tingling sensation

Stop use and ask a doctor if

- you feel eye pain
- changes in vision occur
- redness or irritation of the eye lasts
- condition worsens or lasts more than 72 hours

Keep out of reach of children.

If swallowed, get medical help or contact a Poison Control Center right away. Accidental swallowing by infants and children may lead to coma and marked reduction in body temperature.

Directions

- adults and children 6 years of age and over: put 1 or 2 drops in the affected eye(s) up to 4 times a day
- children under 6 years of age: consult a doctor

Other information

- Store at 15° to 25°C (59° to 77°F)

Inactive ingredients

benzalkonium chloride, boric acid, edetate disodium, purified water, sodium borate, sodium hydroxide and/or hydrochloric acid

Questions?

call toll-free 888-734-7648 or 215-273-8755 (collect)

Distributed by: JOHNSON & JOHNSON CONSUMER INC. Skillman, NJ 08558

PRINCIPAL DISPLAY PANEL - 15 mL Bottle Carton

VISINE ®

NAPHAZOLINE HCl 0.025%

AND PHENIRAMINE MALEATE 0.3%

OPHTHALMIC SOLUTION

ANTIHISTAMINE AND REDNESS RELIEVER

ALLERGY EYE RELIEF

MULTI-ACTION

ORIGINAL

PRESCRIPTION STRENGTH

Clinically Proven to

Relieve Red,

Itchy Eyes

STERILE

EYE DROPS

1/2 FL OZ (15mL)